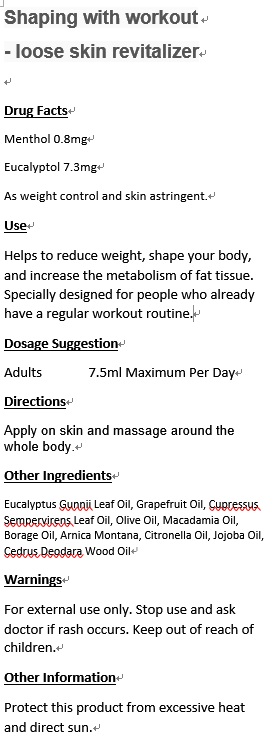 DRUG LABEL: Shaping with workout
NDC: 70470-8002 | Form: OIL
Manufacturer: PHYTOPIA CO., LTD.
Category: otc | Type: HUMAN OTC DRUG LABEL
Date: 20160505

ACTIVE INGREDIENTS: EUCALYPTOL 7.3 mg/50 mL; MENTHOL 0.8 mg/50 mL
INACTIVE INGREDIENTS: JOJOBA OIL; CITRONELLA OIL; EUCALYPTUS GUNNII LEAF OIL; CEDRUS DEODARA WOOD OIL; CUPRESSUS SEMPERVIRENS LEAF OIL; OLIVE OIL; MACADAMIA OIL; BORAGE OIL; ARNICA MONTANA; GRAPEFRUIT OIL

Drug Facts

Menthol 0.8mg

Eucalyptol 7.3mg

As weight control and skin astringent.

Use

Helps to reduce weight, shape your body, and increase the metabolism of fat tissue. Specially designed for people who already have a regular workout routine.

Dosage Suggestion

Adults 7.5ml Maximum Per Day

Directions

Apply on skin and massage around the whole body.

INACTIVE INGREDIENT

Other Ingredients

Eucalyptus Gunnii Leaf Oil, Grapefruit Oil, Cupressus Sempervirens Leaf Oil, Olive Oil, Macadamia Oil, Borage Oil, Arnica Montana, Citronella Oil, Jojoba Oil, Cedrus Deodara Wood Oil

Warnings

For external use only. Stop use and ask doctor if rash occurs. Keep out of reach of children.

Warnings

For external use only. Stop use and ask doctor if rash occurs. Keep out of reach of children.

Other Information

Protect this product from excessive heat and direct sun.

PACKAGE LABEL

Shaping with workout

- loose skin revitalizer